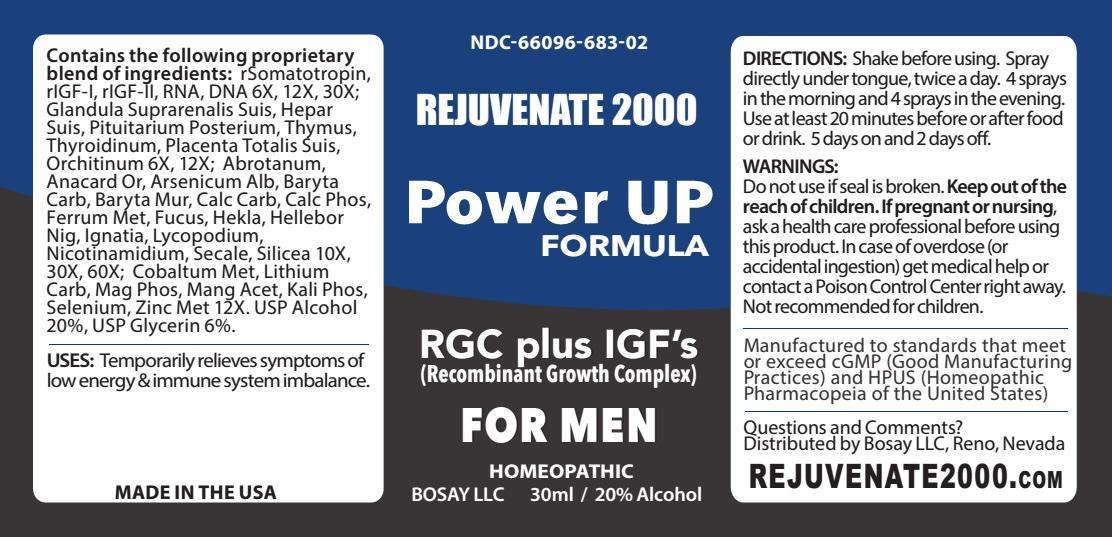 DRUG LABEL: Rejuvenate 2000 Power Up Formula For Men
NDC: 66096-683 | Form: SPRAY
Manufacturer: OHM PHARMA INC.
Category: homeopathic | Type: HUMAN OTC DRUG LABEL
Date: 20130827

ACTIVE INGREDIENTS: SOMATROPIN 6 [hp_X]/30 mL; DALOTUZUMAB 6 [hp_X]/30 mL; SACCHAROMYCES CEREVISIAE RNA 6 [hp_X]/30 mL; HERRING SPERM DNA 6 [hp_X]/30 mL; SUS SCROFA ADRENAL GLAND 6 [hp_X]/30 mL; PORK LIVER 6 [hp_X]/30 mL; SUS SCROFA PITUITARY GLAND 6 [hp_X]/30 mL; SUS SCROFA THYMUS 6 [hp_X]/30 mL; THYROID, UNSPECIFIED 6 [hp_X]/30 mL; SUS SCROFA PLACENTA 6 [hp_X]/30 mL; SUS SCROFA TESTICLE 6 [hp_X]/30 mL; ARTEMISIA ABROTANUM FLOWERING TOP 10 [hp_X]/30 mL; SEMECARPUS ANACARDIUM JUICE 10 [hp_X]/30 mL; ARSENIC TRIOXIDE 10 [hp_X]/30 mL; BARIUM CARBONATE 10 [hp_X]/30 mL; BARIUM CHLORIDE DIHYDRATE 10 [hp_X]/30 mL; OYSTER SHELL CALCIUM CARBONATE, CRUDE 10 [hp_X]/30 mL; TRIBASIC CALCIUM PHOSPHATE 10 [hp_X]/30 mL; IRON 10 [hp_X]/30 mL; FUCUS VESICULOSUS 10 [hp_X]/30 mL; HEKLA LAVA 10 [hp_X]/30 mL; HELLEBORUS NIGER ROOT 10 [hp_X]/30 mL; STRYCHNOS IGNATII SEED 10 [hp_X]/30 mL; LYCOPODIUM CLAVATUM SPORE 10 [hp_X]/30 mL; NIACINAMIDE 10 [hp_X]/30 mL; CLAVICEPS PURPUREA SCLEROTIUM 10 [hp_X]/30 mL; SILICON DIOXIDE 10 [hp_X]/30 mL; COBALT 12 [hp_X]/30 mL; LITHIUM CARBONATE 12 [hp_X]/30 mL; MAGNESIUM PHOSPHATE, DIBASIC TRIHYDRATE 12 [hp_X]/30 mL; MANGANESE ACETATE TETRAHYDRATE 12 [hp_X]/30 mL; POTASSIUM PHOSPHATE, DIBASIC 12 [hp_X]/30 mL; SELENIUM 12 [hp_X]/30 mL; ZINC 12 [hp_X]/30 mL
INACTIVE INGREDIENTS: WATER; ALCOHOL; GLYCERIN

REJUVENATE 2000 POWER UP FORMULA FOR MEN

ACTIVE INGREDIENT

Contains the following proprietary blend of ingredients:

rSomatotropin, rIGF-I, rIGF-II, RNA, DNA 6X, 12X, 30X; Glandula Suprarenalis Suis, Hepar Suis, Pituitarium Posterium, Thymus, Thyroidinum, Placenta Totalis Suis, Orchitinum 6X, 12X; Abrotanum, Anacard Or, Arsenicum Alb, Baryta Carb, Baryta Mur, Calc Carb, Calc Phos, Ferrum Met, Fucus, Hekla, Hellebor Nig, Ignatia, Lycopodium, Nicotinamidium, Secale, Silicea 10X, 30X, 60X; Cobaltum Met, Lithium Carb, Mag Phos, Mang Acet, Kali Phos, Selenium, Zinc Met 12X.

INACTIVE INGREDIENT

USP Alcohol 20%, USP Glycerin 6%.

INDICATIONS AND USAGE

USES: Temporarily relieves symptoms of low energy and immune system imbalance.

DOSAGE AND ADMINISTRATION

DIRECTIONS: Shake before using. Spray directly under tongue, twice a day. 4 sprays in the morning and 4 sprays in the evening. Use at least 20 minutes before or after food or drink. 5 days on and 2 days off.

WARNINGS:

Do not use if seal is broken. Keep out of the reach of children. If pregnant or nursing, ask a health care professional before using this product. In case of overdose (or accidental ingestion) get medical help or contact a Poison Control Center right away. Not recommended for children.

Keep out of the reach of children.

OTHER SAFETY INFORMATION

Manufactured to standards that meet or exceed cGMP (Good Manufacturing Practices) and HPUS (Homeopathic Pharmacopeia of the United States).

OTHER SAFETY INFORMATION

MADE IN THE USA

Questions and Comments?

Distributed by Bosay LLC, Reno, Nevada

REJUVENATE2000.COM

PACKAGE LABEL

NDC-66096-683-02

REJUVENATE 2000
Power UP FORMULA
FOR MEN
RGC plus IGF'S
(Recombinant Growth Complex)
HOMEOPATHIC
BOSAY LLC
30 ml / 20% Alcohol

PURPOSE

RGC plus IGF'S (Recombinant Growth Complex)